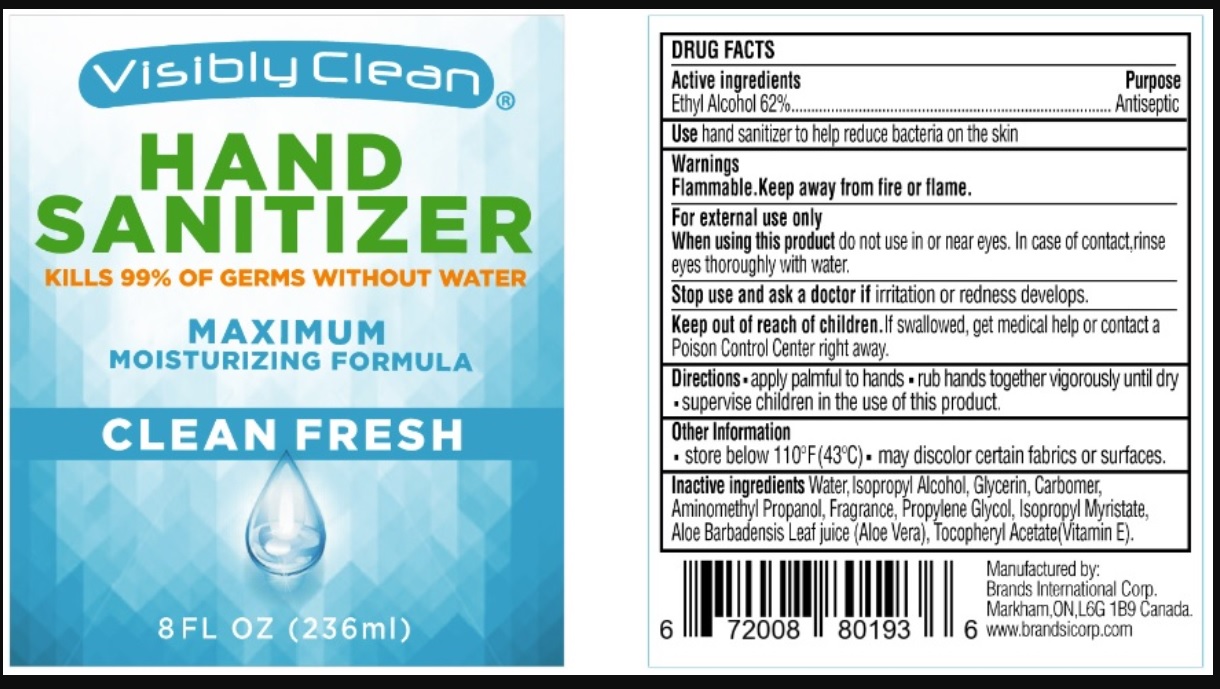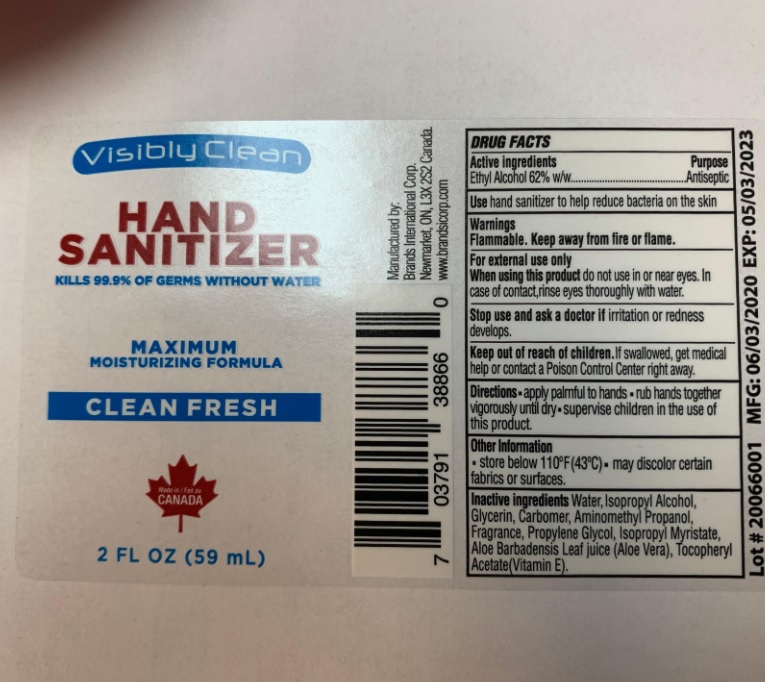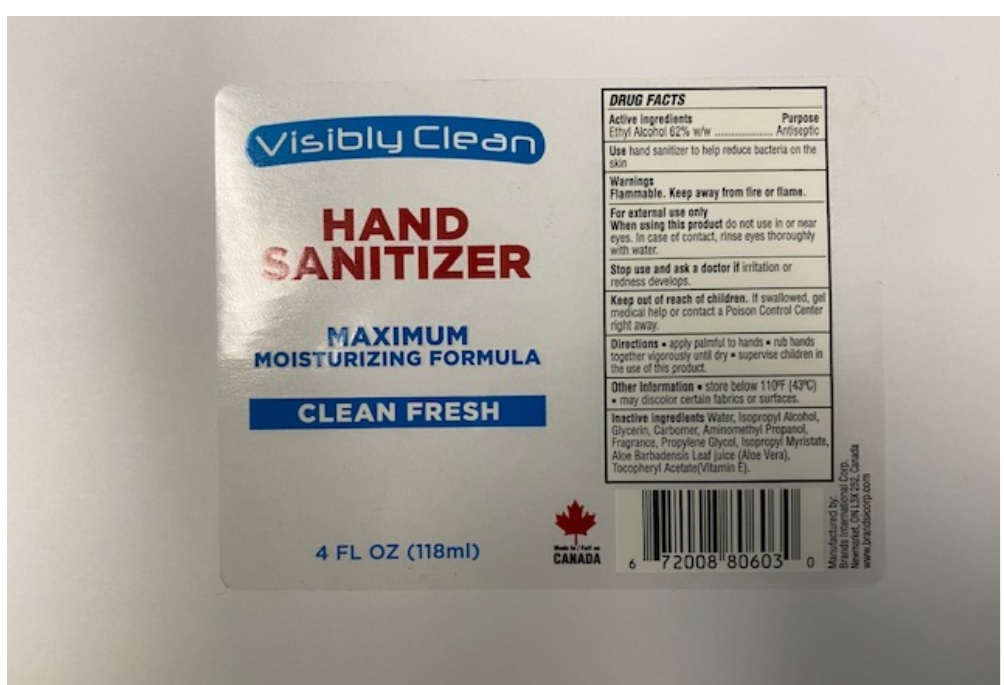 DRUG LABEL: Visibly Clean Hand Sanitizer
NDC: 50157-100 | Form: SOLUTION
Manufacturer: Brands International
Category: otc | Type: HUMAN OTC DRUG LABEL
Date: 20200608

ACTIVE INGREDIENTS: ALCOHOL 62 mL/100 mL
INACTIVE INGREDIENTS: WATER; ISOPROPYL ALCOHOL; GLYCERIN; CARBOMER HOMOPOLYMER TYPE C (ALLYL PENTAERYTHRITOL CROSSLINKED); AMINOMETHYLPROPANOL; ALOE VERA LEAF; .ALPHA.-TOCOPHEROL ACETATE

Visibly Clean Hand Sanitizer

Drug Facts

Active Ingredients

Ethyl Alcohol 62%

Purpose

Antiseptic

Uses

- hand sanitizer to help reuce bacteris on the skin

Warnings

Flammable. Keep away from fire or flame.

For external use only.

When using this product do not use in or near the eyes. In case of eye contact, rinse eyes thoroughly with water.

Stop use and ask a doctor if: irritation and redness develops.

Keep out of reach of children. If swallowed, get medical help or contact a Poison Control Center right away.

Directions

- apply palmful to hands
- rub hands together vigorously until dry
- supervise children in the use of this product.

Other information

- Store below 110°F (43°C)
- May discolor certain fabrics or surfaces.

Inactive ingredients

Water, Isopropyl Alcohol, Glycerin, Carbomer, Aminomethyl Propanol, Fragrance, Propylene Glycol, Isopropyl Myristate, Aloe Barbadensis Leaf juice (Aloe Vera), Tocopheryl Acetate (Vitamin E)

Manufactured by:

Brands International Corp.
Markham, ON, L6G 1B9 Canada
www.brandsicorp.com